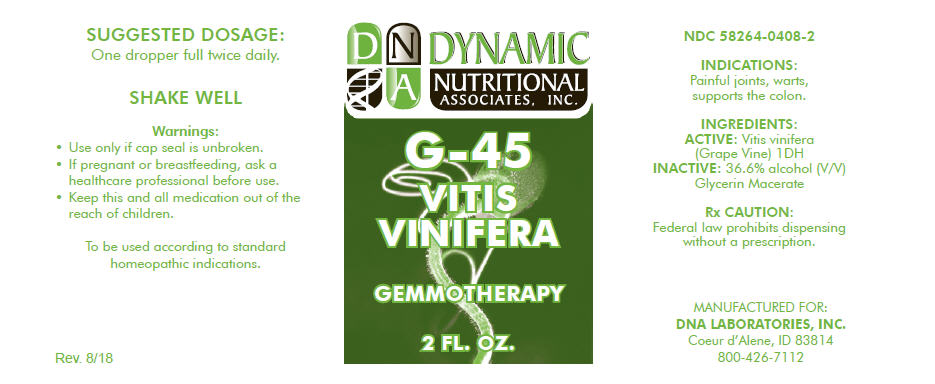 DRUG LABEL: G-45
NDC: 58264-0408 | Form: SOLUTION
Manufacturer: DNA Labs, Inc.
Category: homeopathic | Type: HUMAN OTC DRUG LABEL
Date: 20250109

ACTIVE INGREDIENTS: VITIS VINIFERA FLOWERING TOP 1 [hp_X]/1 mL
INACTIVE INGREDIENTS: ALCOHOL; WATER

G-45

NDC 58264-0408-2

INDICATIONS

PURPOSE

Painful joints, warts, supports the colon.

INGREDIENTS

ACTIVE

Vitis vinifera (Grape Vine) 1DH

INACTIVE

36.6% alcohol (V/V) Glycerin Macerate

Rx CAUTION

Federal law prohibits dispensing without a prescription.

SUGGESTED DOSAGE

One dropper full twice daily.

STORAGE AND HANDLING

SHAKE WELL

Warnings

- Use only if cap seal is unbroken.

PREGNANCY OR BREAST FEEDING

- If pregnant or breastfeeding, ask a healthcare professional before use.

KEEP OUT OF REACH OF CHILDREN

- Keep this and all medication out of the reach of children.

To be used according to standard homeopathic indications.

PRINCIPAL DISPLAY PANEL - 2 FL. OZ. Bottle Label

DYNAMIC
NUTRITIONAL
ASSOCIATES, INC.

G-45

VITIS
VINIFERA

GEMMOTHERAPY

2 FL. OZ.